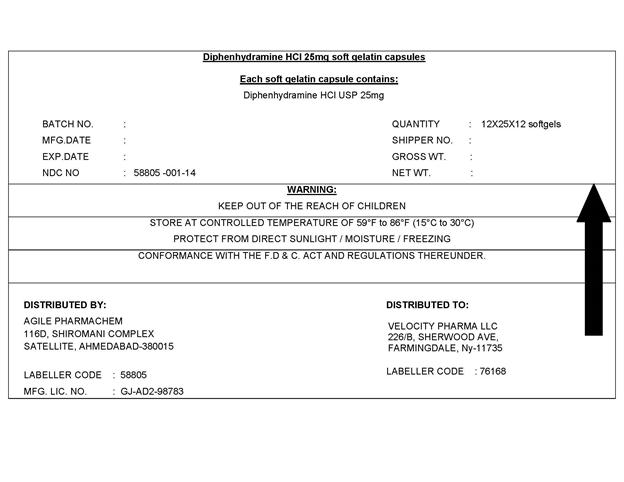 DRUG LABEL: Diphenhydramine Hcl
NDC: 58805-001 | Form: CAPSULE, LIQUID FILLED
Manufacturer: Agile Pharmachem
Category: otc | Type: HUMAN OTC DRUG LABEL
Date: 20140216

ACTIVE INGREDIENTS: DIPHENHYDRAMINE HYDROCHLORIDE 25 mg/1 1
INACTIVE INGREDIENTS: FD&C BLUE NO. 1; FD&C RED NO. 40; GELATIN; GLYCERIN; POLYETHYLENE GLYCOL 1000; SORBITOL

Drug Facts

Active Ingredient

(in each capsule)

Diphenhydramine HCl 25mg

Purpose

Sleep Aid

Uses

- For the relief of occasional sleeplessness
- Reduces time to fall asleep if have difficulty falling asleep

Warnings

Do not use

- If children under 12 years of age
- with any other product containing diphenhydramine, even one used on skin
- with other drug that cause drowsiness such as antihistamines and nighttime cold/flu products
- Do not use with generic NyQuil®

Ask a doctor before use if you have:

- A breathing problem such as asthma, emphysema, or Chronic bronchitis
- glaucoma
- difficulty in urination due to enlargement of the prostate gland
- heart disease
- You are taking a diuretic
  Ask a doctor or pharmacist before use if you are taking sedative or tranquilizers or any other sleep-aid, when using this product :
- Avoid alcoholic beverages and other drugs that cause drowsiness
- Drowsiness will occur
- Be careful when driving a motor vehicle or operating machinery
  Stop use and ask a doctor if sleeplessness persists continuously for more than two weeks.
  Insomnia may be a symptom of serious underlying medical illness.
  If pregnant or breast-feeding, ask a health professional before use.

Keep out of reach of children.

Overdose Warning: Taking more than directed can cause serious health problems, In case of overdose, get medical help or contact a Poison Control Center right away.

Directions

Take only one dose per day (24 hours)- see Overdose warning.

Adults and Children 12 years and over

- One Dose = Two 25 mg LiquiCaps (50 mg) at bedtime if needed or as directed by a doctor

Other Information

- Store at 20-25°C (68-77°F)
- Avoid excessive heat above 40°C(104°F) and high humidity
- Protect from light

Inactive Ingredients

FD&C Blue No. 1, FD&C Red No. 40, Gelatin, Glycerin, Polyethylene Glycol, Purified Water, Sorbitol, Titanium Dioxide

Questions?

Call 1-855-314-1850

TAMPER EVIDENT: This Package is safety sealed & child resistant. Use only if blisters are intact. If difficult to open, use scissors.

PACKAGE LABEL.PRINCIPAL DISPLAY PANEL

NDC: 58805-001-14 LIQUID GELS